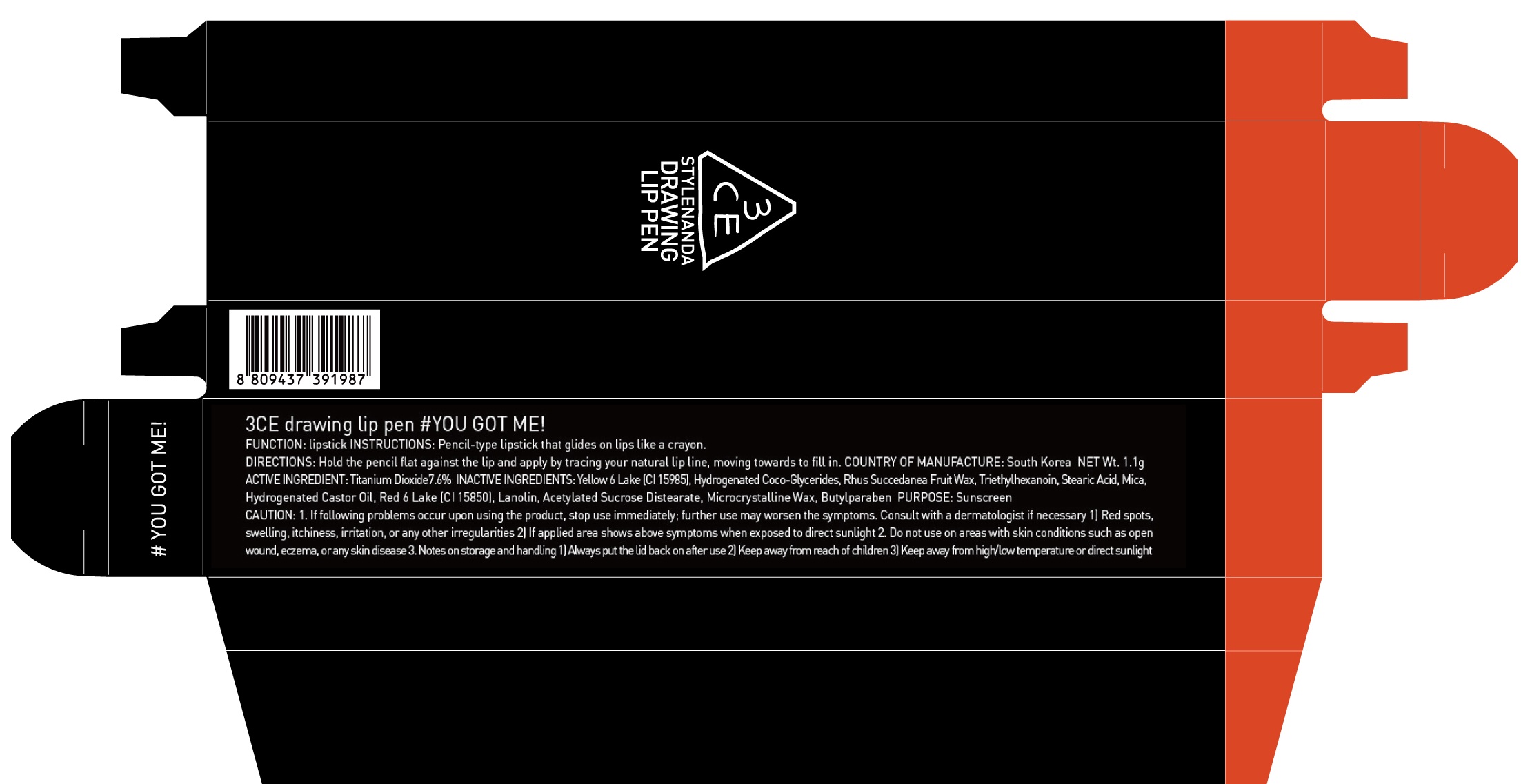 DRUG LABEL: 3CE DRAWING LIP YOU GOT ME
NDC: 60764-110 | Form: LIPSTICK
Manufacturer: Nanda Co., Ltd
Category: otc | Type: HUMAN OTC DRUG LABEL
Date: 20161013

ACTIVE INGREDIENTS: Titanium Dioxide 0.08 g/1.1 g
INACTIVE INGREDIENTS: Triethylhexanoin; Stearic Acid

ACTIVE INGREDIENT

Active Ingredient: Titanium Dioxide 7.6%

INACTIVE INGREDIENT

Inactive Ingredients: Yellow 6 Lake (CI 15985), Hydrogenated Coco-Glycerides, Rhus Succedanea Fruit Wax, Triethylhexanoin, Stearic Acid, Mica, Hydrogenated Castor Oil, Red 6 Lake (CI 15850), Lanolin, Acetylated Sucrose Distearate, Microcrystalline Wax, Butylparaben

PURPOSE

Purpose: Sunscreen

CAUTION

CAUTION: 1. If following problems occur upon using the product, stop use immediately; further use may worsen the symptoms. Consult with a dermatologist if necessary. 1) Red spots, swelling, itchiness, irritation, or any other irregularities. 2) If applied area shows above symptoms when exposed to direct sunlight. 2. Do not use on areas with skin conditions such as open wound, eczema, or any skin disease. 3. Notes on storage and handling 1) Always put the lid back on after use 2) Keep away from reach of children 3) Keep away from high/low temperature or direct sunlight

DESCRIPTION

INSTRUCTIONS: Pencil-type lipstick that glides on lips like a crayon.

Directions: Hold the pencil flat against the lip and apply by tracing your natural lip line, moving towards to fill in.